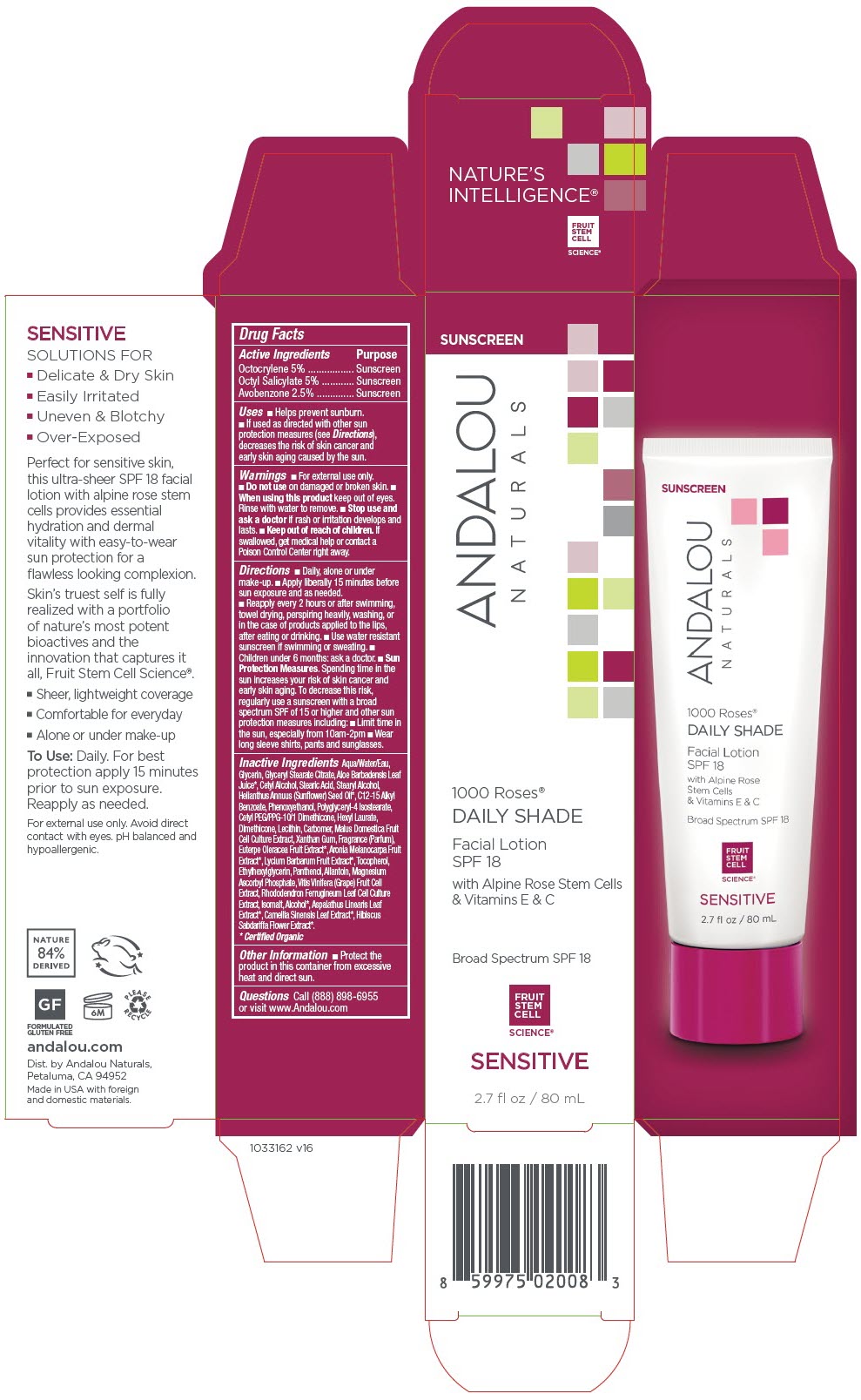 DRUG LABEL: 1000 Roses Daily Shade Facial SPF 18
NDC: 55560-0103 | Form: LOTION
Manufacturer: Andalou naturals
Category: otc | Type: HUMAN OTC DRUG LABEL
Date: 20250609

ACTIVE INGREDIENTS: OCTISALATE 50 mg/1 mL; OCTOCRYLENE 50 mg/1 mL; AVOBENZONE 25 mg/1 mL
INACTIVE INGREDIENTS: WATER; GLYCERIN; GLYCERYL STEARATE CITRATE; ALOE VERA LEAF; CETYL ALCOHOL; STEARIC ACID; STEARYL ALCOHOL; SUNFLOWER OIL; ALKYL (C12-15) BENZOATE; PHENOXYETHANOL; POLYGLYCERYL-4 ISOSTEARATE; CETYL PEG/PPG-10/1 DIMETHICONE (HLB 2); HEXYL LAURATE; DIMETHICONE; SOYBEAN LECITHIN; CARBOMER HOMOPOLYMER TYPE A (ALLYL PENTAERYTHRITOL CROSSLINKED); APPLE; XANTHAN GUM; ACAI; ARONIA MELANOCARPA FRUIT JUICE; LYCIUM BARBARUM FRUIT; TOCOPHEROL; ETHYLHEXYLGLYCERIN; PANTHENOL; ALLANTOIN; MAGNESIUM ASCORBYL PHOSPHATE; VITIS VINIFERA HIGH TANNIN CULTIVAR FRUIT CELL LYSATE; RHODODENDRON FERRUGINEUM LEAF; ISOMALT; ALCOHOL; ASPALATHUS LINEARIS LEAF; TEA LEAF; HIBISCUS SABDARIFFA FLOWER

1000 Roses® Daily Shade Facial Lotion SPF 18

Drug Facts

ACTIVE INGREDIENT

Active Ingredients | Purpose
Octocrylene 5% | Sunscreen
Octyl Salicylate 5% | Sunscreen
Avobenzone 2.5% | Sunscreen

Uses

- Helps prevent sunburn.
- If used as directed with other sun protection measures (see Directions), decreases the risk of skin cancer and early skin aging caused by the sun.

Warnings

- For external use only.

- Do not use on damaged or broken skin.

- When using this product keep out of eyes. Rinse with water to remove.

- Stop use and ask a doctor if rash or irritation develops and lasts.

- Keep out of reach of children. If swallowed, get medical help or contact a Poison Control Center right away.

Directions

- Daily, alone or under make-up.
- Apply liberally 15 minutes before sun exposure and as needed.
- Reapply every 2 hours or after swimming, towel drying, perspiring heavily, washing, or in the case of products applied to the lips, after eating or drinking.
- Use water resistant sunscreen if swimming or sweating.
- Children under 6 months: ask a doctor.
- Sun Protection Measures. Spending time in the sun increases your risk of skin cancer and early skin aging. To decrease this risk, regularly use a sunscreen with a broad spectrum SPF of 15 or higher and other sun protection measures including:
  - Limit time in the sun, especially from 10am-2pm
  - Wear long sleeve shirts, pants and sunglasses.

Inactive Ingredients

Aqua/Water/Eau, Glycerin, Glyceryl Stearate Citrate, Aloe Barbadensis Leaf Juice [Certified Organic] , Cetyl Alcohol, Stearic Acid, Stearyl Alcohol, Helianthus Annuus (Sunflower) Seed Oil, C12-15 Alkyl Benzoate, Phenoxyethanol, Polyglyceryl-4 Isostearate, Cetyl PEG/PPG-10/1 Dimethicone, Hexyl Laurate, Dimethicone, Lecithin, Carbomer, Malus Domestica Fruit Cell Culture Extract, Xanthan Gum, Fragrance (Parfum), Euterpe Oleracea Fruit Extract, Aronia Melanocarpa Fruit Extract, Lycium Barbarum Fruit Extract, Tocopherol, Ethylhexylglycerin, Panthenol, Allantoin, Magnesium Ascorbyl Phosphate, Vitis Vinifera (Grape) Fruit Cell Extract, Rhododendron Ferrugineum Leaf Cell Culture Extract, Isomalt, Alcohol, Aspalathus Linearis Leaf Extract, Camellia Sinensis Leaf Extract, Hibiscus Sabdariffa Flower Extract.

Other Information

- Protect the product in this container from excessive heat and direct sun.

Questions

Call (888) 898-6955 or visit www.Andalou.com

Dist. by Andalou Naturals,
Petaluma, CA 94952

PRINCIPAL DISPLAY PANEL - 80 mL Tube Carton

SUNSCREEN

ANDALOU
NATURALS

1000 Roses®
DAILY SHADE

Facial Lotion
SPF 18

with Alpine Rose Stem Cells
& Vitamins E & C

Broad Spectrum SPF 18

FRUIT
STEM
CELL
SCIENCE®

SENSITIVE

2.7 fl oz / 80 mL